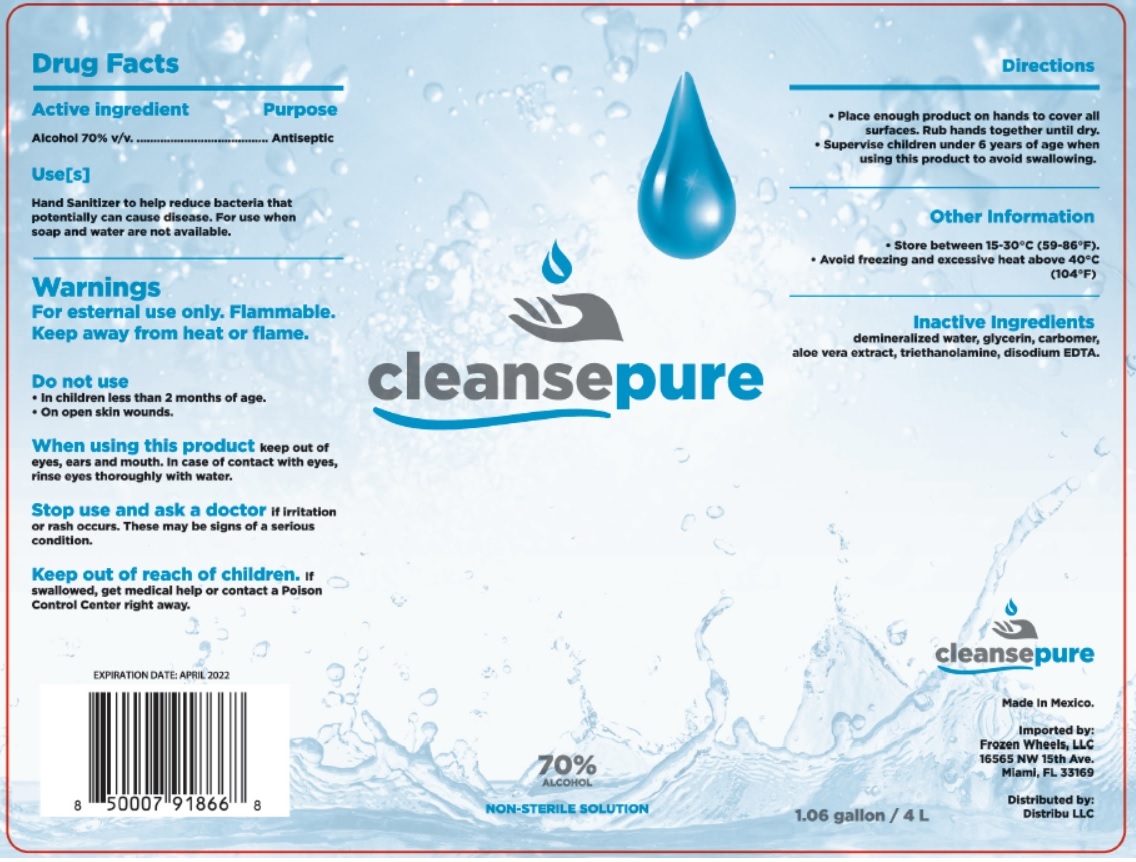 DRUG LABEL: Cleanse pure
NDC: 77031-505 | Form: SOLUTION
Manufacturer: Frozen Wheels, Llc
Category: otc | Type: HUMAN OTC DRUG LABEL
Date: 20200605

ACTIVE INGREDIENTS: ALCOHOL 70 mL/100 mL
INACTIVE INGREDIENTS: WATER; GLYCERIN; CARBOMER HOMOPOLYMER, UNSPECIFIED TYPE; ALOE VERA LEAF; TROLAMINE; EDETATE DISODIUM ANHYDROUS

cleansepure

Active ingredient

Alcohol 70% v/v.

Purpose

Antiseptic

Use[s]

Hand Sanitizer to help reduce bacteria that potentially can cause disease. For use when soap and water are not available.

Warnings

For external use only. Flammable.

Keep away from heat or flame.

Do not use

- In children less than 2 months of age.
- On open skin wounds.

When using this product keep out of eyes, ears, and mouth. In case of contact with eyes, rinse eyes thoroughly with water.

Stop use and ask a doctor if irritation or rash occurs. These may be signs of a serious condition.

Keep out of reach of children If swallowed, get medical help or contact a Poison Control Center right away.

Directions

- Place enough product on hands to cover all surfaces. Rub hands together until dry.
- Supervise children under 6 years of age when using this product to avoid swallowing.

Other Information

- Store between 15-30°C (59-86°F).
- Avoid freezing and excessive heat above 40°C (104°F).

Inactive Ingredients

demineralized water, glycerin, carbomer, aloe vera extract, triethanolamine, disodium EDTA.

NON-STERILE SOLUTION

Made in Mexico.

Imported by:

Frozen Wheels, LLC

16565 NW 15th Ave.

Miami, FL 33169

Distributed by:

Distribu LLC